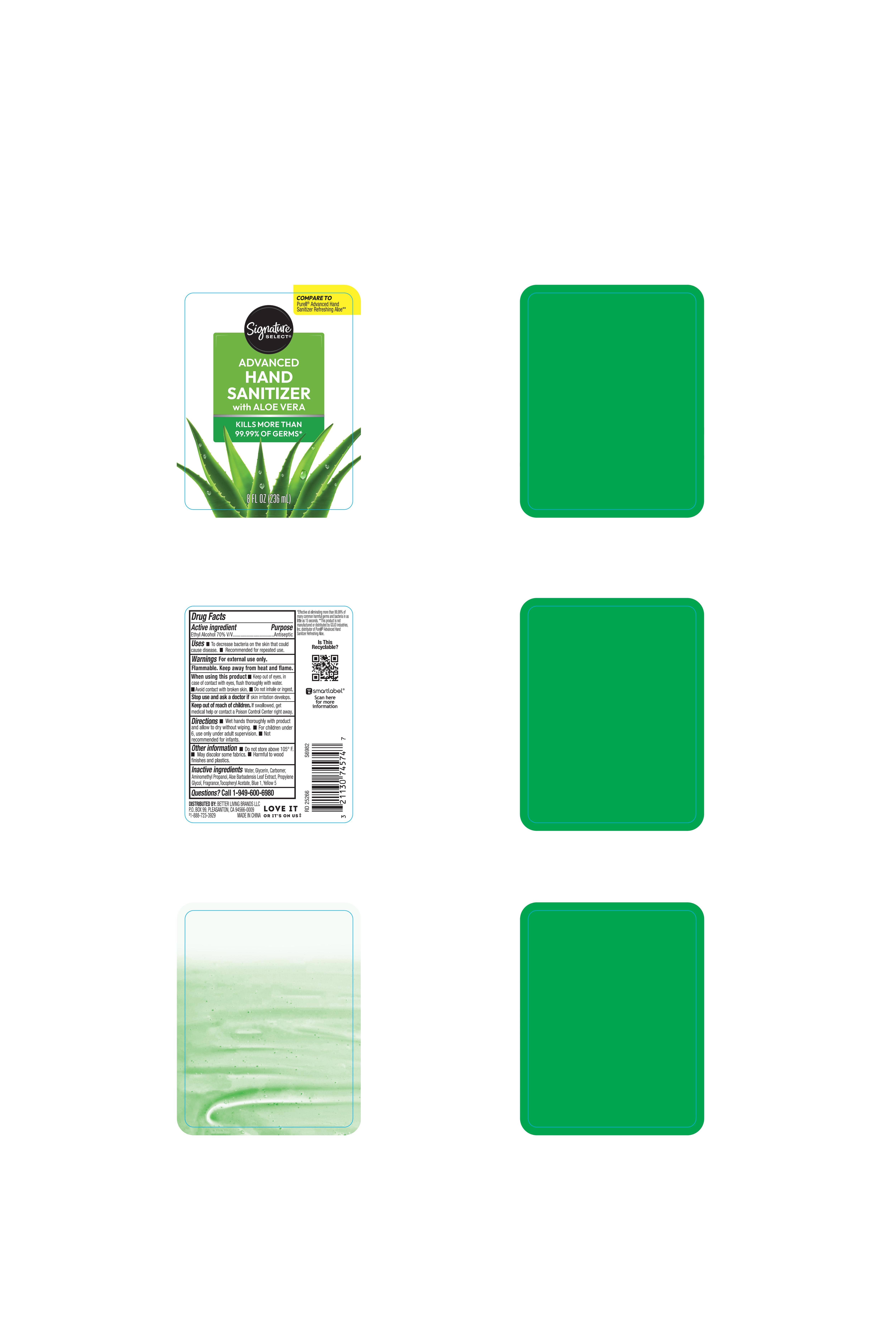 DRUG LABEL: Signature Select Advanced Hand Sanitizer with Aloe Vera
NDC: 21130-066 | Form: SOLUTION
Manufacturer: Living Better Brands LLC
Category: otc | Type: HUMAN OTC DRUG LABEL
Date: 20260126

ACTIVE INGREDIENTS: ALCOHOL 70 mL/100 mL
INACTIVE INGREDIENTS: WATER; ALOE BARBADENSIS LEAF JUICE; GLYCERIN; CARBOMER; AMINOMETHYL PROPANOL; PROPYLENE GLYCOL; .ALPHA.-TOCOPHEROL ACETATE; FD&C YELLOW NO. 5; FD&C BLUE NO. 1

21130-066 Alcohol sanitizer with Aloe

Active ingredient

Ethyl Alcohol 70% v/v

Purpose

Antiseptic

Uses

- To decrease bacteria on the skin that could cause disease
- Recommended for repeated use

Warnings

For external use only.

Flammable, keep away from fire or flame

When using this product

Keep out of eyes. In case of contact with eyes, flush thoroughly with water

Avoid contact with broken skin

Do not inhale or ingest

Stop use and ask a doctor if skin irritation develops

Keep out of reach of children. If swallowed, get medical help or contact a Poison Control Center right away.

Directions:

- Wet hands thoroughly with product and allow to dry without wiping
- For children under 6, use only under adult supervision
- Not recommended for infants

Other Information

- Do not store above 105F
- May discolor some fabrics
- Harmful for wood finishes and plastics

Inactive ingredients

Water, Glycerin, Carbomer, Aminomethyl Propanol, Aloe Barbadensis Leaf Extract, Propylene Glycol, Fragrance, Tocopheryl Acetate, Blue 1, Yellow 5